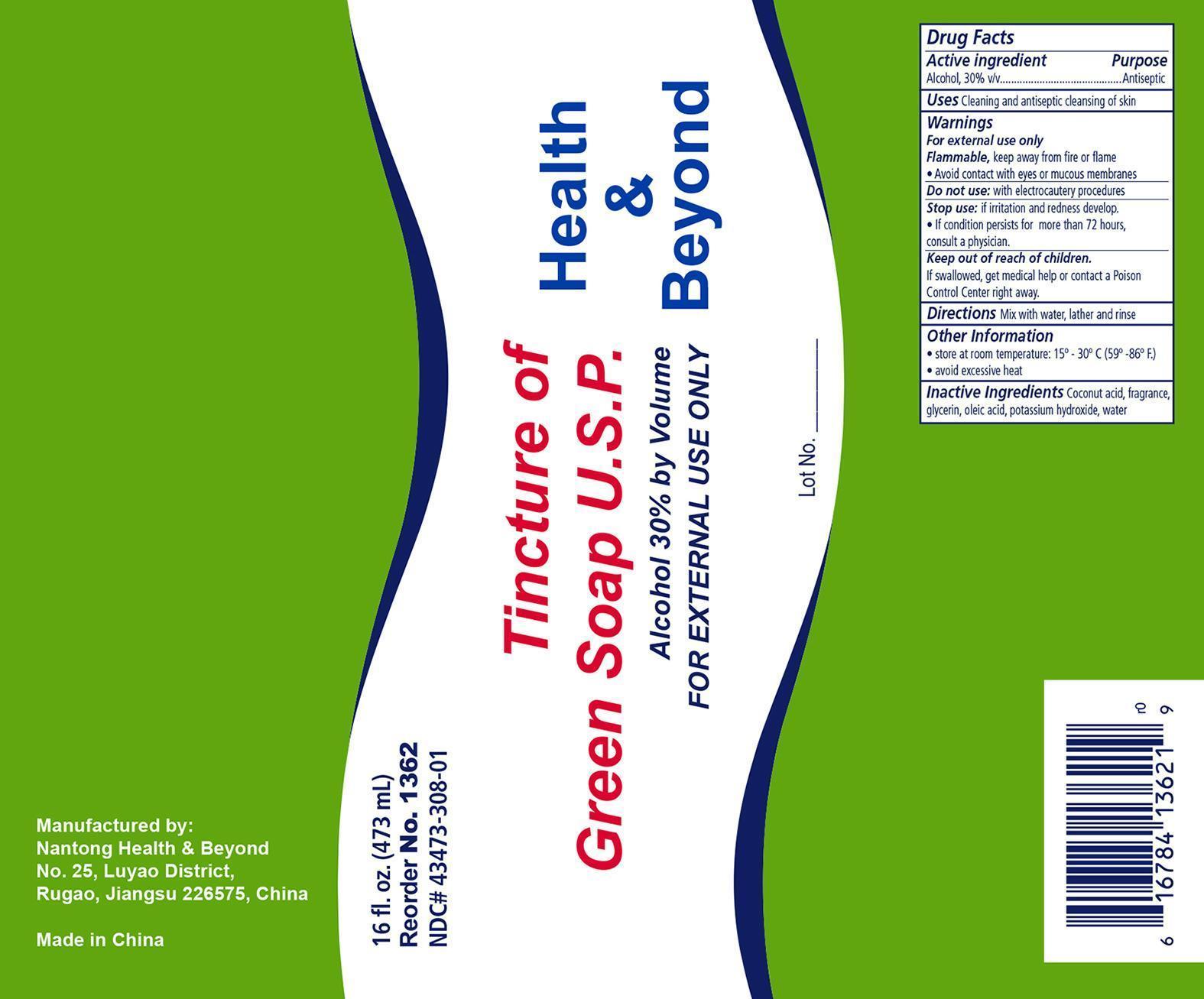 DRUG LABEL: Health and Beyond Green
NDC: 43473-308 | Form: LIQUID
Manufacturer: Nantong Health & Beyond Hygienic Products Inc
Category: otc | Type: HUMAN OTC DRUG LABEL
Date: 20141208

ACTIVE INGREDIENTS: ALCOHOL 0.30 mL/1 mL
INACTIVE INGREDIENTS: OLEIC ACID; POTASSIUM HYDROXIDE; WATER; COCONUT ACID; GLYCERIN

Nantong Health & Beyond Green Soap

ACTIVE INGREDIENT

Active Ingredient Purpose

Alcohol, 30% v/v Antiseptic

WARNINGS

- For external use only
- Flammable, keep away from fire or flame
- Avoid contact with eyes and mucousal membranes

Do not use with electrocautery procedures

PURPOSE

An antiseptic wash.

INDICATIONS & USAGE

Cleaning and antiseptic cleansing of skin.

DOSAGE & ADMINISTRATION

Mix with water, lather and rinse off.

KEEP OUT OF REACH OF CHILDREN, if swallowed get medical help or contact a Poison Control Center right away.

OTHER INFORMATION

- Store at room temperature: 15o - 30o C (59o - 86o F)
- Avoid excessive heat

INACTIVE INGREDIENTS

Inactive ingredients: Coconut acid, Fragrance, Glycerin, oleic acid, potassium hydroxide, water.

PRINCIPAL DISPLAY PANEL

Nantong Health & Beyond Green Soap

HB Green Soap.jpg